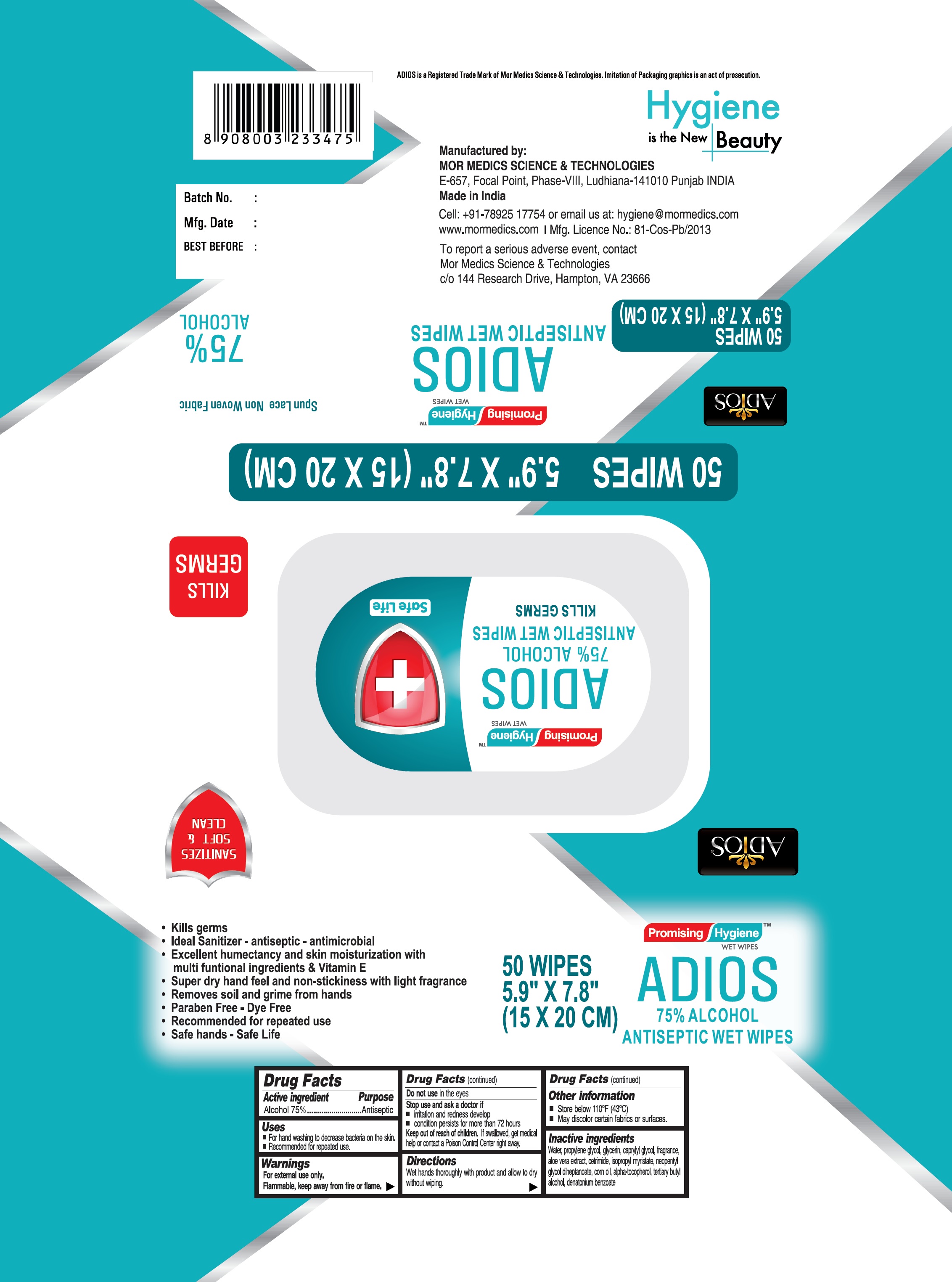 DRUG LABEL: ADIOS Antiseptic Wet Wipes
NDC: 81138-001 | Form: CLOTH
Manufacturer: MOR MEDICS SCIENCE & TECHNOLOGIES
Category: otc | Type: HUMAN OTC DRUG LABEL
Date: 20210428

ACTIVE INGREDIENTS: ALCOHOL 75 g/100 g
INACTIVE INGREDIENTS: WATER; PROPYLENE GLYCOL; GLYCERIN; CAPRYLYL GLYCOL; ALOE VERA LEAF; CETRIMIDE; ISOPROPYL MYRISTATE; NEOPENTYL GLYCOL DIHEPTANOATE; CORN OIL; ALPHA-TOCOPHEROL; TERT-BUTYL ALCOHOL; DENATONIUM BENZOATE

ADIOS Antiseptic Wet Wipes

Active ingredient

Alcohol 75%

Purpose

Antiseptic

Uses

- For hand washing to decrease bacteria on the skin.
- Recommended for repeated use.

Warnings

For external use only.
Flammable, keep away from fire or flame.

Do not use

in the eyes

Stop use and ask a doctor if

- irritation and redness develop
- condition persists for more than 72 hours

Keep out of reach of children.

If swallowed, get medical help or contact a Poison Control Center right away.

Directions

Wet hands thoroughly with product and allow to dry without wiping.

Other information

- Store below 110°F (43°C)
- May discolor certain fabrics or surfaces.

Inactive ingredients

Water, propylene glycol, glycerin, caprylyl glycol, fragrance, aloe vera extract, cetrimide, isopropyl myristate, neopentyl glycol diheptanoate, corn oil, alpha-tocopherol, tertiary butyl alcohol, denatonium benzoate